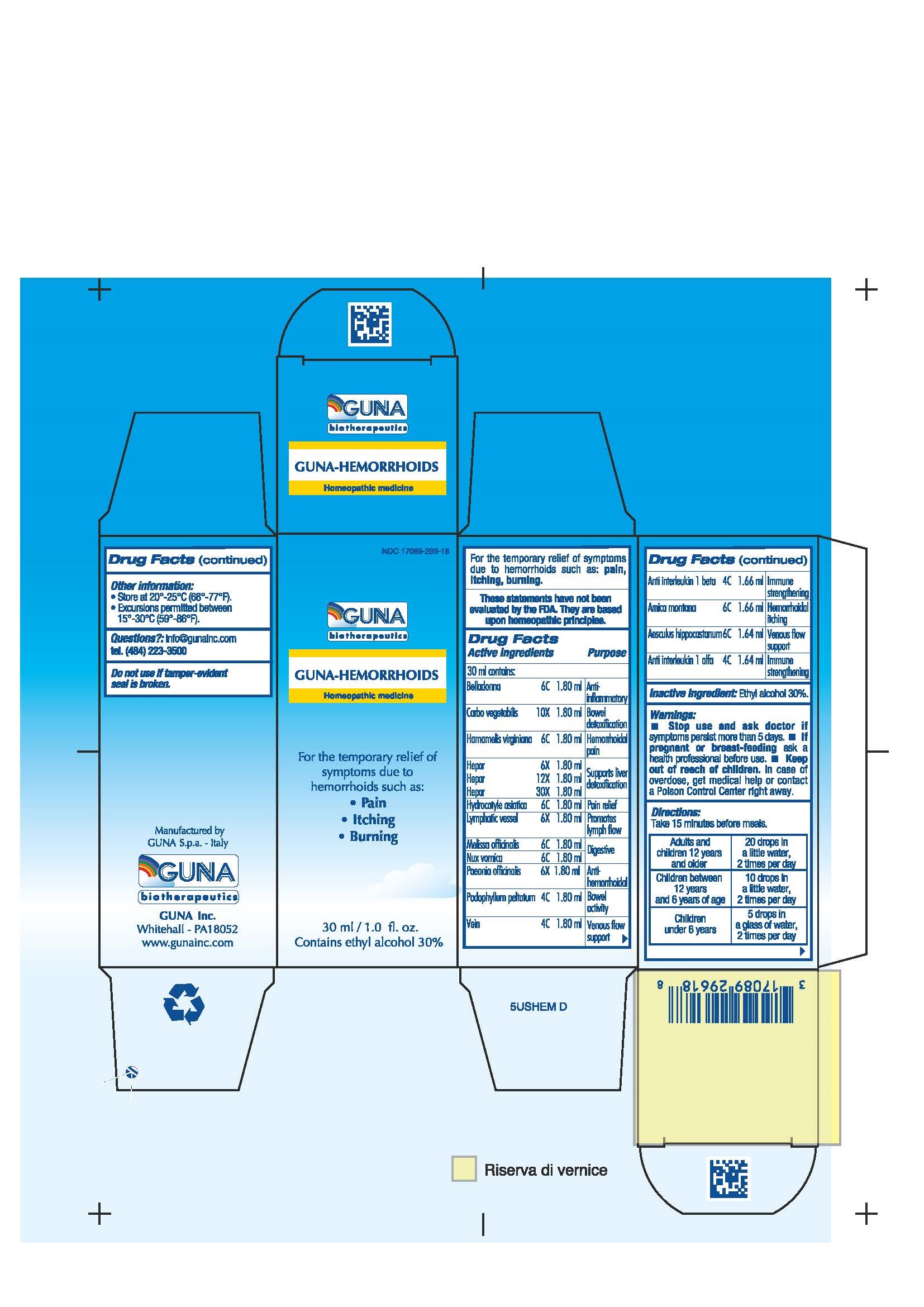 DRUG LABEL: GUNA-HEMORRHOIDS
NDC: 17089-296 | Form: SOLUTION/ DROPS
Manufacturer: Guna spa
Category: homeopathic | Type: HUMAN OTC DRUG LABEL
Date: 20181221

ACTIVE INGREDIENTS: AESCULUS HIPPOCASTANUM FLOWER 6 [hp_C]/30 mL; ANTI-INTERLEUKIN-1.ALPHA. IMMUNOGLOBULIN G RABBIT 4 [hp_C]/30 mL; CANAKINUMAB 4 [hp_C]/30 mL; ARNICA MONTANA 6 [hp_C]/30 mL; ATROPA BELLADONNA 6 [hp_C]/30 mL; ACTIVATED CHARCOAL 10 [hp_X]/30 mL; HAMAMELIS VIRGINIANA ROOT BARK/STEM BARK 6 [hp_C]/30 mL; PORK LIVER 12 [hp_X]/30 mL; HYDROCOTYLE ASIATICA EXTRACT 6 [hp_C]/30 mL; SUS SCROFA SMALL INTESTINE MUCOSA LYMPH FOLLICLE 6 [hp_X]/30 mL; MELISSA OFFICINALIS 6 [hp_C]/30 mL; STRYCHNOS NUX-VOMICA SEED 6 [hp_C]/30 mL; PAEONIA OFFICINALIS ROOT 6 [hp_X]/30 mL; PODOPHYLLUM PELTATUM ROOT 4 [hp_C]/30 mL; SUS SCROFA VEIN 4 [hp_C]/30 mL
INACTIVE INGREDIENTS: ALCOHOL 9 mL/30 mL

GUNA-HEMORRHOIDS

ACTIVE INGREDIENTS/PURPOSE

AESCULUS HIPPOCASTANUM 6C VENOUS FLOW SUPPORT
ANTI INTERLEUKIN 1 ALPHA 4C IMMUNE STRENGTHENING
ANTI INTERLEUKIN 1 BETA 4C IMMUNE STRENGTHENING
ARNICA MONTANA 6C HEMORRHOIDAL ITCHING
BELLADONNA 6C ANTI-INFLAMMATORY
CARBO VEGETALIS 10X BOWEL DETOXIFICATION
HAMAMELIS VIRGINIANA 6C HEMORRHOIDAL PAIN
HEPAR 6X, 12X, 30X SUPPORTS LIVER DETOXIFICATION
HYDROCOTYLE ASIATICA 6C PAIN RELIEF
LYMPHATIC VESSEL 6X PROMOTES LYMPH FLOW
MELISSA OFFICINALIS 6C DIGESTIVE
NUX VOMICA 6C DIGESTIVE
PAEONIA OFFICINALIS 6X ANTIHEMORRHOIDAL
PODOPHYLLUM PELTATUM 4C BOWEL ACTIVITY
VEIN 4C VENOUS FLOW SUPPORT

USES

Temporary relief of symptoms due to hemorrhoids such as:

- Pain
- Itching
- Burning

WARNINGS

Stop use and ask doctor if symptoms persist more than 5 days.
If pregnant or breast-feeding ask a health professional before use.
Keep out of reach of children. In case of overdose, get medical help or contact a Poison Control Center right away.
Contains ethyl alcohol 30%

PREGNANCY

If pregnant or breast-feeding ask a doctor before use.

WARNINGS

Keep out of reach of children.

DIRECTIONS

Adults and children 12 years and older 20 drops in a little water, 2 times per day
Children between 12 years and 6 years of age 10 drops in a little water, 2 times per day
Children under 6 years 5 drops in a glass of water, 2 times per day

QUESTIONS

Questions?: info@gunainc.com, tel. (484) 223-3500

INDICATIONS AND USAGE

Take 15 minutes before meals.

Inactive ingredient: Ethyl alcohol 30%.